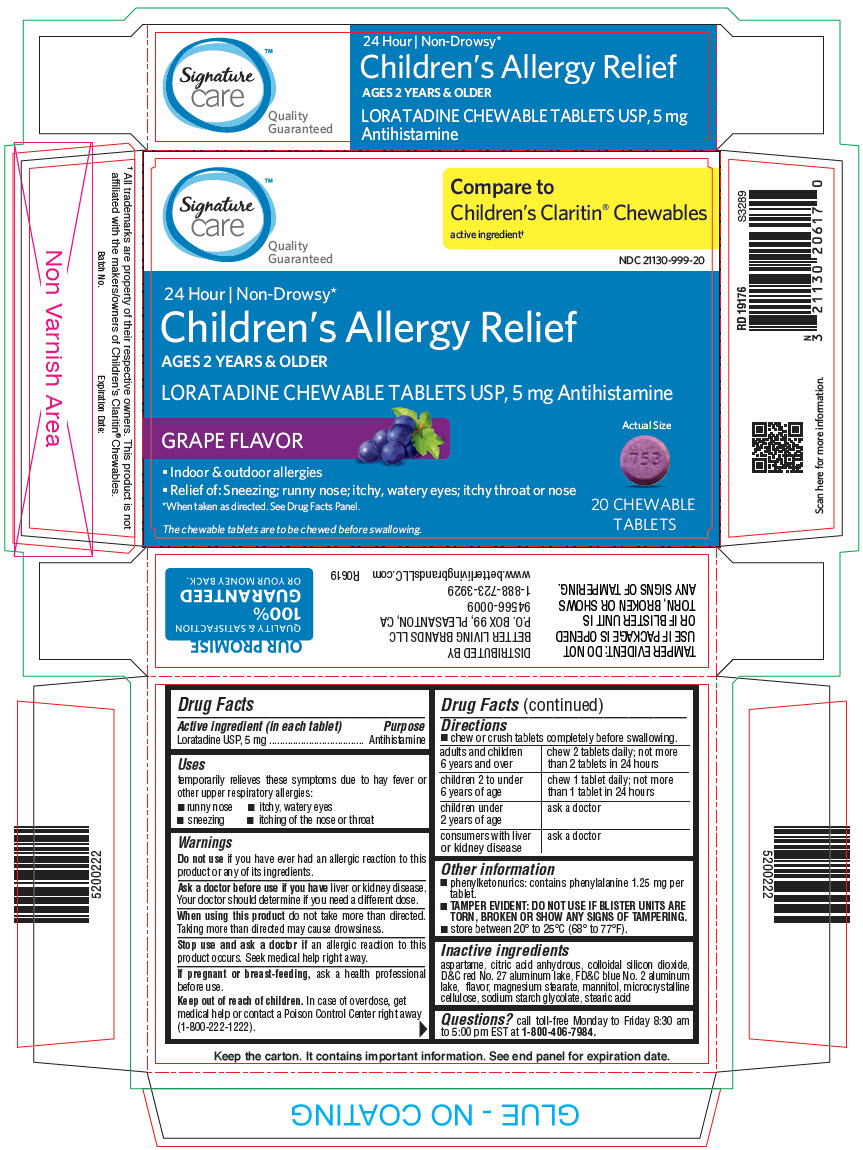 DRUG LABEL: CHILDRENS LORATADINE
NDC: 21130-999 | Form: TABLET, CHEWABLE
Manufacturer: SAFEWAY
Category: otc | Type: HUMAN OTC DRUG LABEL
Date: 20241229

ACTIVE INGREDIENTS: LORATADINE 5 mg/1 1
INACTIVE INGREDIENTS: ASPARTAME; ANHYDROUS CITRIC ACID; SILICON DIOXIDE; D&C RED NO. 27; FD&C BLUE NO. 2; MAGNESIUM STEARATE; MANNITOL; MICROCRYSTALLINE CELLULOSE; SODIUM STARCH GLYCOLATE TYPE A POTATO; STEARIC ACID

CHILDREN'S LORATADINE

Drug Facts

Active ingredient (in each tablet)

Loratadine USP, 5 mg

Purpose

Antihistamine

Uses

temporarily relieves these symptoms due to hay fever or other upper respiratory allergies:

- runny nose
- itchy, watery eyes
- sneezing
- itching of the nose or throat

Warnings

DO NOT USE

Do not useif you have ever had an allergic reaction to this product or any of its ingredients.

Ask a doctor before use if you haveliver or kidney disease. Your doctor should determine if you need a different dose.

WHEN USING

When using this productdo not take more than directed. Taking more than directed may cause drowsiness.

Stop use and ask a doctor ifan allergic reaction to this product occurs. Seek medical help right away.

PREGNANCY OR BREAST FEEDING

If pregnant or breast-feeding,ask a health professional before use.

Keep out of reach of children.In case of overdose, get medical help or contact a Poison Control Center right away (1-800-222-1222).

Directions

- chew or crush tablets completely before swallowing.

adults and children 6 years and over | chew 2 tablets daily; not more than 2 tablets in 24 hours
children 2 to under 6 years of age | chew 1 tablet daily; not more than 1 tablet in 24 hours
children under 2 years of age | ask a doctor
consumers with liver or kidney disease | ask a doctor

Other information

- phenylketonurics: contains phenylalanine 1.25 mg per tablet.
- TAMPER EVIDENT: DO NOT USE IF BLISTER UNITS ARE TORN, BROKEN OR SHOW ANY SIGNS OF TAMPERING.
- store between 20° to 25°C (68° to 77°F).

Inactive ingredients

aspartame, citric acid anhydrous, colloidal silicon dioxide, D&C red No. 27 aluminum lake, FD&C blue No. 2 aluminum lake, flavor, magnesium stearate, mannitol, microcrystalline cellulose, sodium starch glycolate, stearic acid

Questions?

call toll-free Monday to Friday 8:30 am to 5:00 pm EST at 1-800-406-7984.

DISTRIBUTED BY
BETTER LIVING BRANDS LLC
P.O. BOX 99, PLEASANTON, CA
94566-0009

PRINCIPAL DISPLAY PANEL - 5 mg Tablet Blister Pack Carton

Signature
care™
Quality
Guaranteed

Compare to
Children's Claritin®Chewables
active ingredient†

NDC 21130-999-20

24 Hour | Non-Drowsy*

Children's Allergy Relief

AGES 2 YEARS & OLDER

LORATADINE CHEWABLE TABLETS USP, 5 mg Antihistamine

GRAPE FLAVOR

Actual Size

- Indoor & outdoor allergies
- Relief of: Sneezing; runny nose; itchy, watery eyes; itchy throat or nose

*When taken as directed. See Drug Facts Panel.

The chewable tablets are to be chewed before swallowing.

20 CHEWABLE
TABLETS